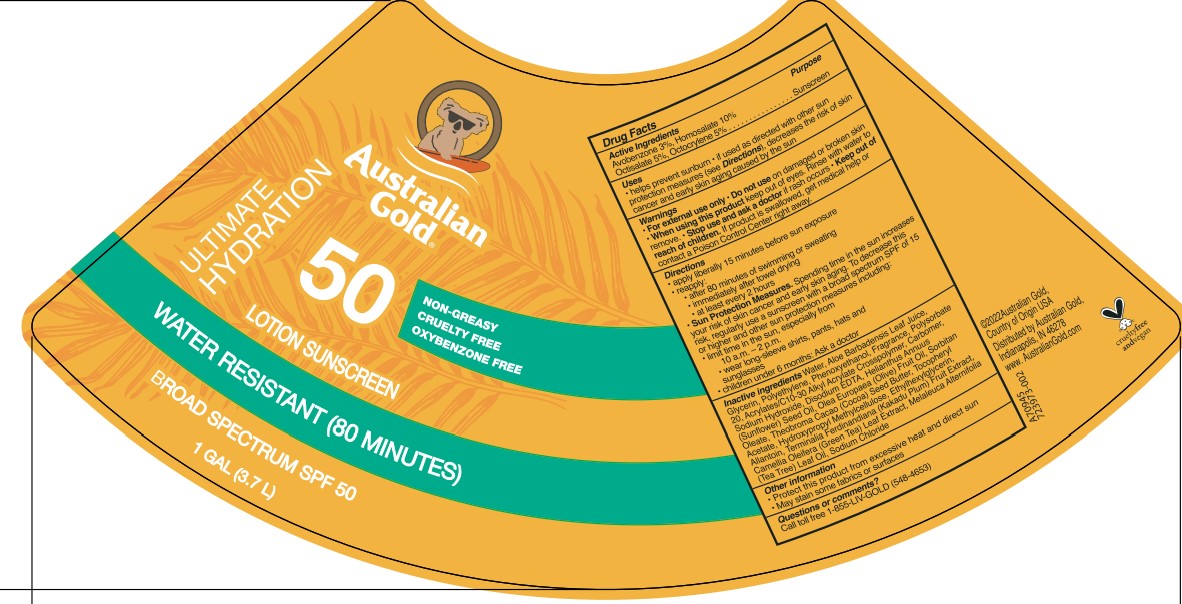 DRUG LABEL: Australian Gold
NDC: 58443-0566 | Form: LOTION
Manufacturer: Prime Enterprises, Inc.
Category: otc | Type: HUMAN OTC DRUG LABEL
Date: 20220906

ACTIVE INGREDIENTS: AVOBENZONE 29.43 mg/1 mL; HOMOSALATE 98.1 mg/1 mL; OCTISALATE 49.1 mg/1 mL; OCTOCRYLENE 49.1 mg/1 mL
INACTIVE INGREDIENTS: CARBOMER HOMOPOLYMER, UNSPECIFIED TYPE; ALOE VERA LEAF; GLYCERIN; PHENOXYETHANOL; HIGH DENSITY POLYETHYLENE; POLYSORBATE 20; COCOA BUTTER; SORBITAN MONOOLEATE; .ALPHA.-TOCOPHEROL ACETATE; WATER; SODIUM HYDROXIDE; ETHYLHEXYLGLYCERIN; CARBOMER INTERPOLYMER TYPE A (55000 CPS); EDETATE DISODIUM ANHYDROUS; HYPROMELLOSES; CAMELLIA OLEIFERA LEAF; TEA TREE OIL; KAKADU PLUM; ALLANTOIN; SUNFLOWER OIL; OLIVE OIL; SODIUM CHLORIDE

Australian Gold Broad Spectrum SPF 50 Sunscreen Lotion

Active Ingredients

Avobenzone 3 %, Homosalate 10 %, Octisalate 5 %, Octocrylene 5 %

Purpose

Sunscreen

Uses

- helps prevent sunburn
- if used as directed with other sun protection measures (see Directions), decreases the risk of skin cancer and early skin aging caused by the sun

Warnings

For external use only

Do not use on damaged or broken skin

When using this product keep out of eyes. Rinse with water to remove.

Stop use and ask a doctor if rash occurs.

Keep out of reach of children. If product is swallowed, get medical help or contact a Poison Control Center right away.

Directions

- apply liberally 15 minutes before sun exposure
- reapply:
  - after 80 minutes of swimming or sweating
  - immediately after towel drying
  - at least every 2 hours
- Sun Protection Measures. Spending time in the sun increases your risk of skin cancer and early skin aging. To decease this risk, regularly use a sunscreen with a broad spectrum SPF of 15 or higher and other sun protection measures including:
  - limit time in the sun, especially from 10 a.m. – 2 p.m.
  - wear long-sleeve shirts, pants, hats, and sunglasses
- children under 6 months: Ask a doctor

Inactive Ingredients

Water, Glycerin, Polyethylene, Phenoxyethanol, Fragrance, Polysorbate 20, Acrylates/C10-30 Alkyl Acrylate Crosspolymer, Carbomer, Sodium Hydroxide, Disodium EDTA, Helianthus Annuus (Sunflower) Seed Oil, Hydroxypropyl Methylcellulose, Olea Europaea (Olive) Fruit Oil, Sorbitan Oleate, Theobroma Cacao (Cocoa) Seed Butter, Tocopheryl Acetate, Ethylhexylglycerin, Allantoin, Aloe Barbadensis Leaf Juice, Camellia Oleifera (Green Tea) Leaf Extract, Melaleuca Alternifolia (Tea Tree) Leaf Oil, Terminalia Ferdinandiana (Kakadu Plum) Fruit Extract

Other information

- Protect this product from excesive heat and direct sun
- May stain some fabrics or surfaces

Questions or Comments?

Call toll free 1-855-LIV-GOLD (548-4653)